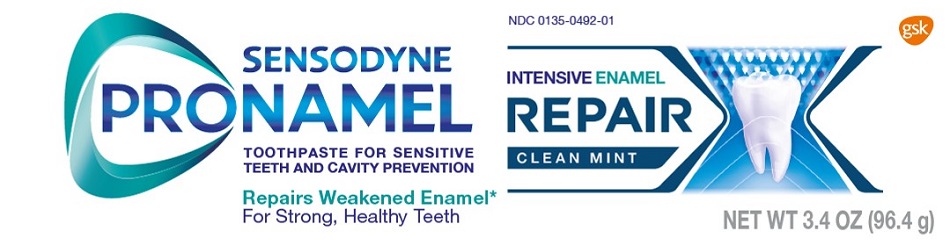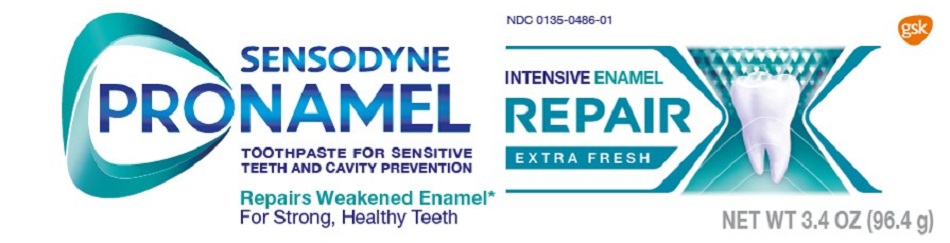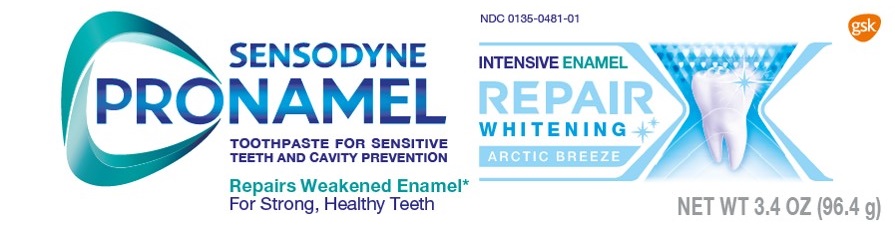 DRUG LABEL: SENSODYNE PRONAMEL

NDC: 0135-0492 | Form: PASTE
Manufacturer: Haleon US Holdings LLC
Category: otc | Type: HUMAN OTC DRUG LABEL
Date: 20240409

ACTIVE INGREDIENTS: POTASSIUM NITRATE 50 mg/1 g; SODIUM FLUORIDE 1.15 mg/1 g
INACTIVE INGREDIENTS: WATER; SORBITOL; HYDRATED SILICA; GLYCERIN; POLYETHYLENE GLYCOL 400; SODIUM LACTATE; COCAMIDOPROPYL BETAINE; TITANIUM DIOXIDE; XANTHAN GUM; SACCHARIN SODIUM; SODIUM HYDROXIDE

Drug Facts

Active ingredients

Potassium nitrate 5%

Sodium fluoride 0.25% (0.15% w/v fluoride ion)

Purposes

Antihypersensitivity

Anticavity

Uses

- builds increasing protection against painful sensitivity of the teeth to cold, heat, acids, sweets, or contact.
- aids in the prevention of dental cavities.

Warnings

When using this product,

if irritation occurs discontinue use.

Stop use and ask a dentist if

- the problem persists or worsens. Sensitive teeth may indicate a serious problem that may need prompt care by a dentist.
- pain/sensitivity still persists after 4 weeks of use.

Keep out of reach of children.

If more than used for brushing is accidentally swallowed, get medical help or contact a Poison Control Center right away.

Directions

- adults and children 12 years of age and older:
  - apply at least a 1-inch strip of the product onto a soft bristle toothbrush.
  - brush teeth thoroughly for at least 1 minute twice a day (morning and evening), and not more than 3 times a day, or as recommended by a dentist or doctor. Make sure to brush all sensitive areas of the teeth. Minimize swallowing. Spit out after brushing.
- children under 12 years of age:Consult a dentist or doctor.

Other information

- do not store above 25°C (77°F)

Inactive ingredients

water, sorbitol, hydrated silica, glycerin, PEG-8, sodium lactate, flavor, cocamidopropyl betaine, titanium dioxide, xanthan gum, sodium saccharin, PVM/MA copolymer, sodium hydroxide

Questions or comments?

1-866-844-2797

Principal Display Panel

NDC 0135-0492-01

SENSODYNE

PRONAMEL

INTENSIVE ENAMEL REPAIR

TOOTHPASTE FOR SENSITIVE TEETH AND CAVITY PREVENTION

CLEAN MINT

Repairs Weakened Enamel*

For Strong, Healthy Teeth

NET WT 3.4 OZ (96.4 g)

SENSODYNEPRONAMEL

INTENSIVE ENAMEL REPAIR

* Sensodyne Pronamel Intensive Enamel Repairis proven to drive minerals deepinto the enamel surface to help actively repairacid-weakened areas of the enamel, for stronger, better-protected teeth.

PRONAMEL ACTIVELY REPAIRS WEAKENED ENAMEL

LOCKS IN MINERALS

FOR STRONG HEALTHY TEETH

Acids in modern diets can weaken your enamel surface. Over time, this can lead to your enamel thinning, allowing the yellow dull dentin layer underneath to show through. Once your enamel surface is weakened it needs extra care for the future.

With twice-daily brushing, Sensodyne Pronamel Intensive Enamel Repair helps to:

- Actively repair acid-weakened enamel
- Lock in minerals to protect against the effects of acid wear
- Protect against cavities

Sensodyne Pronamel Intensive Enamel Repair is suitable for sensitive teeth.

Recycle Carton, Tube and Cap

Save Water Turn off tap while brushing

ALWAYS FOLLOW THE LABEL

Trademarks owned or licensed by GSK. ©2022 GSK or licensor.

Distributed by: GSK Consumer Healthcare, Warren, NJ 07059

62000000069608 Front Carton

Principal Display Panel

NDC 0135-0486-01

SENSODYNE

PRONAMEL

INTENSIVE ENAMEL REPAIR

TOOTHPASTE FOR SENSITIVE TEETH AND CAVITY PREVENTION

EXTRA FRESH

Repairs Weakened Enamel*

For Strong, Healthy Teeth

NET WT 3.4 OZ (96.4 g)

SENSODYNE

PRONAMEL

INTENSIVE ENAMEL REPAIR

* Sensodyne Pronamel Intensive Enamel Repairis proven to drive minerals deepinto the enamel surface to help actively repairacid-weakened areas of the enamel, for stronger, better-protected teeth.

PRONAMEL ACTIVELY REPAIRS WEAKENED ENAMEL

LOCKS IN MINERALS

FOR STRONG HEALTHY TEETH

Acids in modern diets can weaken your enamel surface. Over time, this can lead to your enamel thinning, allowing the yellow dull dentin layer underneath to show through. Once your enamel surface is weakened it needs extra care for the future.

With twice-daily brushing, Sensodyne Pronamel Intensive Enamel Repair helps to:

- Actively repair acid-weakened enamel
- Lock in minerals to protect against the effects of acid wear
- Protect against cavities

Sensodyne Pronamel Intensive Enamel Repair is suitable for sensitive teeth.

Recycle Carton, Tube and Cap

Save Water Turn off tap while brushing

ALWAYS FOLLOW THE LABEL

Trademarks owned or licensed by GSK. ©2022 GSK or licensor.

Distributed by: GSK Consumer Healthcare, Warren, NJ 07059

62000000068911 Front Carton

Principal Display Panel

NDC 0135-0481-01

SENSODYNE

PRONAMEL

INTENSIVE ENAMEL REPAIR

TOOTHPASTE FOR SENSITIVE TEETH AND CAVITY PREVENTION

WHITENING ARTIC BREEZE

Repairs Weakened Enamel*

For Strong, Healthy Teeth

NET WT 3.4 OZ (96.4 g)

SENSODYNE

PRONAMEL

INTENSIVE ENAMEL REPAIR

WHITENING

* Sensodyne Pronamel Intensive Enamel Repairis proven to drive minerals deepinto the enamel surface to help actively repairacid-weakened areas of the enamel, for stronger, better-protected teeth.

PRONAMEL ACTIVELY REPAIRS WEAKENED ENAMEL

LOCKS IN MINERALS

FOR STRONG HEALTHY TEETH

Acids in modern diets can weaken your enamel surface. Over time, this can lead to your enamel thinning, allowing the yellow dull dentin layer underneath to show through. Once your enamel surface is weakened it needs extra care for the future.

With twice-daily brushing, Sensodyne Pronamel Intensive Enamel Repair helps to:

- Actively repair acid-weakened enamel
- Lock in minerals to protect against the effects of acid wear
- Protect against cavities

Sensodyne Pronamel Intensive Enamel Repair is suitable for sensitive teeth.

Recycle Carton, Tube and Cap

Save Water Turn off tap while brushing

ALWAYS FOLLOW THE LABEL

Trademarks owned or licensed by GSK. ©2022 GSK or licensor.

Distributed by: GSK Consumer Healthcare, Warren, NJ 07059

62000000068993 Front Carton